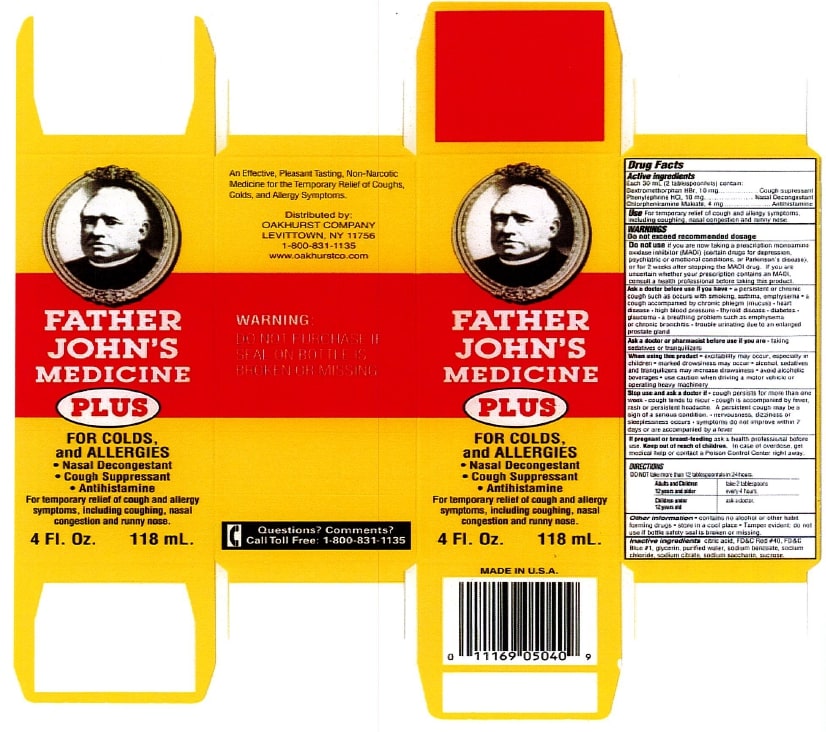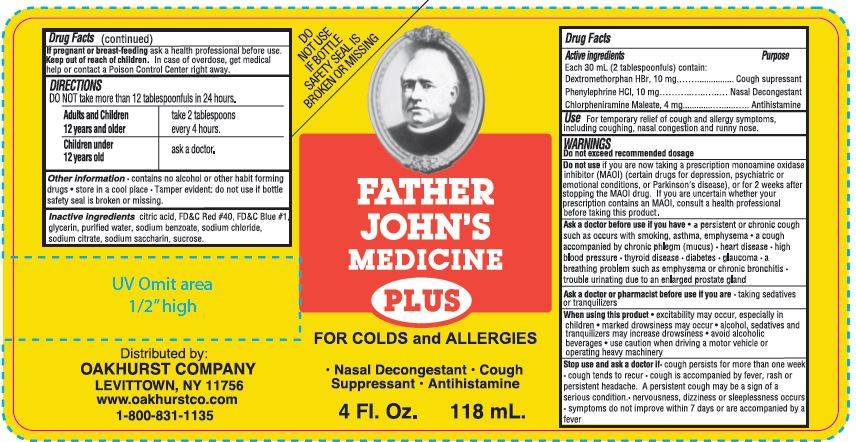 DRUG LABEL: Father Johns Cough Medicine Plus
NDC: 45728-445 | Form: LIQUID
Manufacturer: Oakhurst Company
Category: otc | Type: HUMAN OTC DRUG LABEL
Date: 20231218

ACTIVE INGREDIENTS: DEXTROMETHORPHAN HYDROBROMIDE 10 mg/30 mL; PHENYLEPHRINE HYDROCHLORIDE 10 mg/30 mL; CHLORPHENIRAMINE MALEATE 4 mg/30 mL
INACTIVE INGREDIENTS: SACCHARIN SODIUM; SUCROSE; GLYCERIN; ANHYDROUS CITRIC ACID; FD&C RED NO. 40; FD&C BLUE NO. 1; SODIUM CHLORIDE; WATER; SODIUM CITRATE; SODIUM BENZOATE

Father John's Medicine Plus

ACTIVE INGREDIENT

Each 30 mL (2 tablespoonfuls) contain:

Dextromethorphan HBr, 10mg

Phenylephrine HCl, 10mg

Chlorpheniramine Maleate, 4mg

INACTIVE INGREDIENT

Citric acid

FD&C Red #40

FD&C Blue #1

Glycerin

Purified water

Sodium benzoate

Sodium chloride

Sodium citrate

Sodium saccharin

Sucrose

DOSAGE AND ADMINISTRATION

DO NOT take more than 12 tablespoonfuls in 24 hours

Adults and Children 12 years and older: take 2 tablespoons every 4 hours

Children under 12 years old: ask a doctor

INDICATIONS AND USAGE

For temporarily relief of couch and allergy symptoms, including coughing, nasal congestion, and runny nose.

WARNINGS: Do not excees recommended dosage

PURPOSE

Cough Supressant

Nasal Decongestant

Anthihistamine

Keep out of reach of children. In case of overdose, get medical help or contact a Poison Control Center right away.

PACKAGE LABEL

'